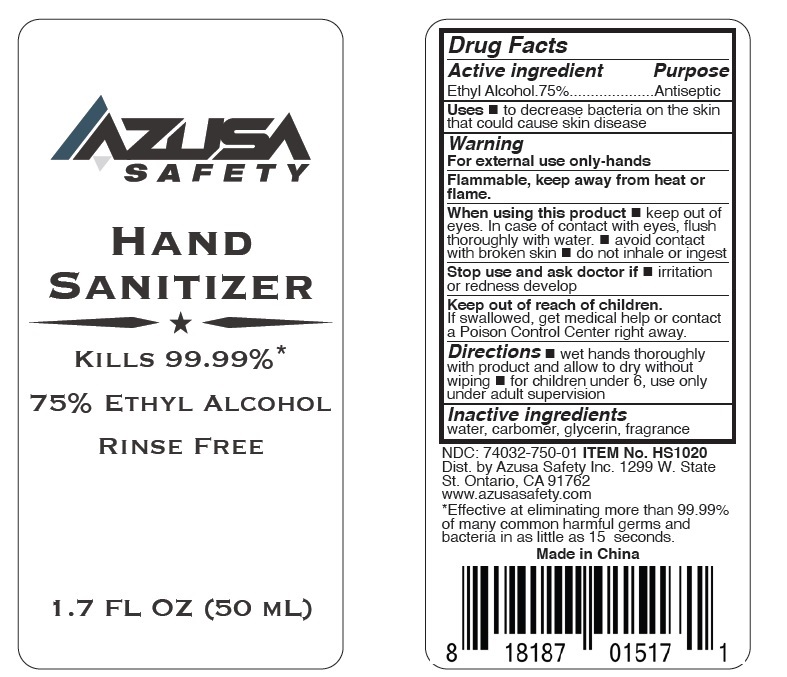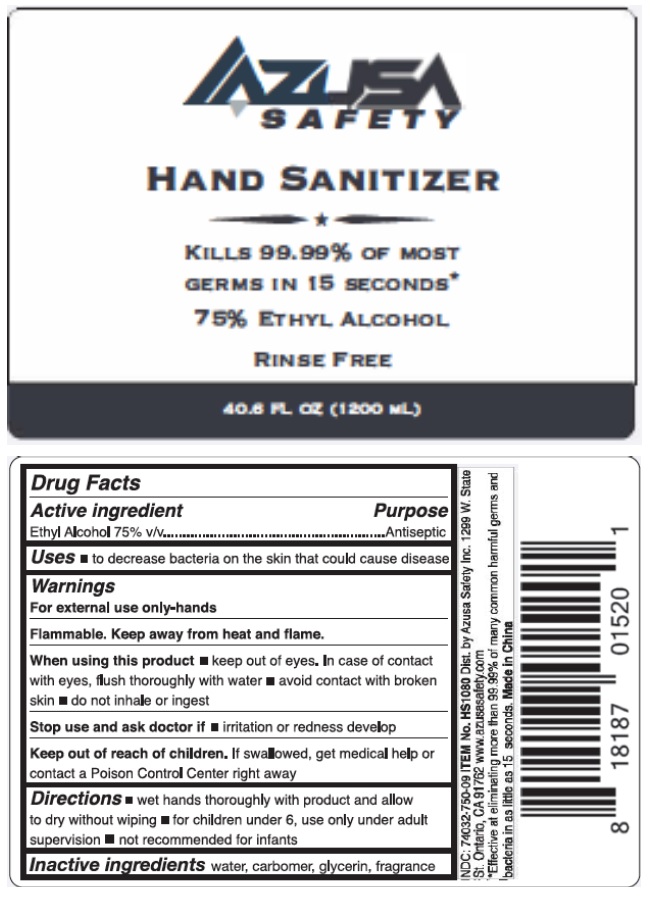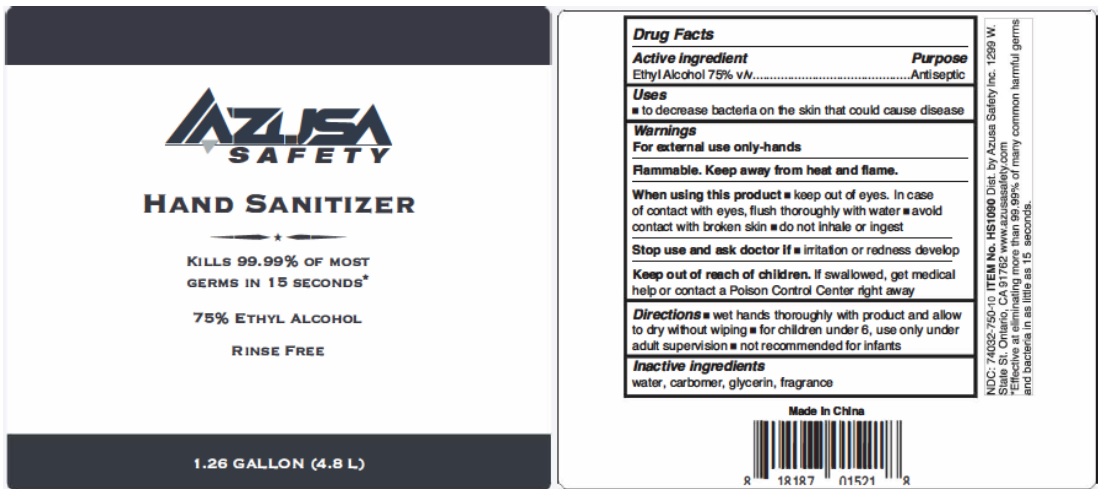 DRUG LABEL: AZUSA SAFETY HAND SANITIZER
NDC: 74032-750 | Form: GEL
Manufacturer: Azusa Safety, Inc.
Category: otc | Type: HUMAN OTC DRUG LABEL
Date: 20200728

ACTIVE INGREDIENTS: ALCOHOL 75 mL/100 mL
INACTIVE INGREDIENTS: WATER; CARBOMER HOMOPOLYMER, UNSPECIFIED TYPE; GLYCERIN; TROLAMINE

AZUSA SAFETY HAND SANITIZER

Active ingredient

Ethyl Alcochol 75%

Purpose

Antiseptic

Uses

to decrease bacteria on the skin that could cause skin disease.

Warning

For external use only-hands

Flammable, keep away from heat or flame.

When using this product

- Keep out of eyes. In case of contact with eyes, flush thoroughly with water
- avoid contact with broken skin
- do not inhale or ingest

Stop use and ask doctor if irritation or redness develop

Keep out of reach of children.

If swallowed, get medical help or contact a Poison Control Center right away.

Directions

- wet hands thoroughly with product and allow to dry without wiping
- for children under 6, use only under adult supervision

Inactive ingredients

water, carbomer, glycerin, fragrance

KILLS 99.99% *
RINSE FREE

Dist. by Azusa Safety, Inc. 1299 W. State
St Ontario, CA 91762
www.azusasafety.com

*Effective at eliminating more than 99.99% of many common harmful germs and bacteria in as little as 15 seconds.

Made in China